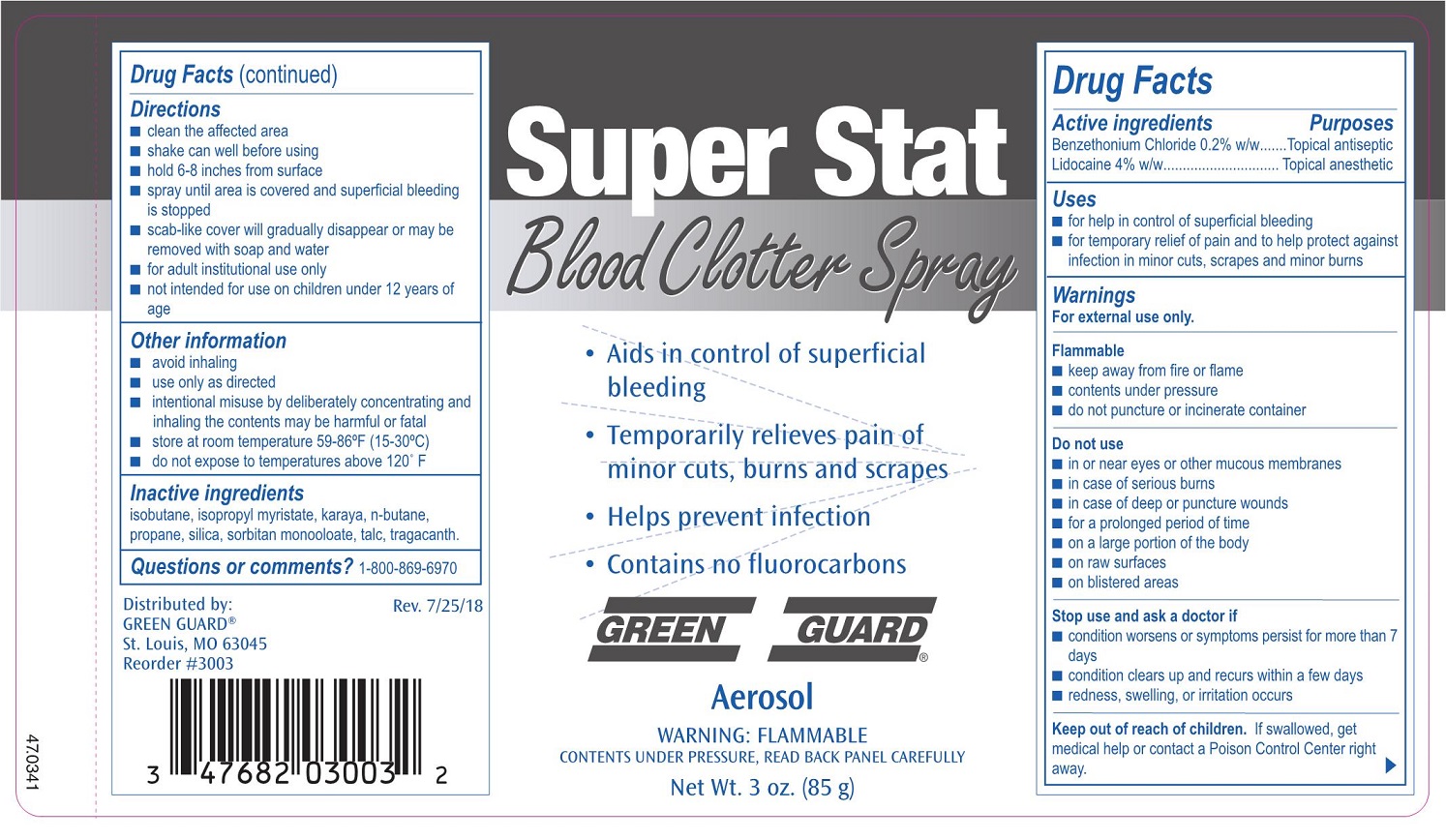 DRUG LABEL: Green Guard Super Stat Blood Clotting First Aid
NDC: 47682-300 | Form: AEROSOL, SPRAY
Manufacturer: Unifirst First Aid Corporation
Category: otc | Type: HUMAN OTC DRUG LABEL
Date: 20250908

ACTIVE INGREDIENTS: LIDOCAINE 3400 mg/85 g; BENZETHONIUM CHLORIDE 170 mg/85 g
INACTIVE INGREDIENTS: ISOBUTANE; ISOPROPYL MYRISTATE; KARAYA GUM; BUTANE; PROPANE; SILICON DIOXIDE; SORBITAN MONOOLEATE; TALC; TRAGACANTH

Green Guard Super Stat Blood Clotter Spray

Active Ingredients

Benzethonium Chloride 0.2% w/w
Lidocaine 4% w/w

Purpose

Topical Antiseptic
Topical Anesthetic

Uses

- for help on control of superificial bleeding
- for temporary relief of pain and to help protect against infection in minor cuts, scrapesand minor burns
- minor burns

Warnings

For external use only.

Flammable

- keep away from flame
- contents under pressure
- do not puncture or incinerate container

Do not use

- in or near eyes or other mucous membranes
- in case of serious burns
- in case of deep or puncture wounds
- for a prolonged period of time
- on large portions of the body
- on raw surfaces
- on blistered areas

Stop use and ask a doctor if

- condition worsens or symptoms persist for more than 7 days
- condition clars up and recurs within a few days
- redness, swelling, or irritation occurs

Keep out of reach of children.

If swallowed, get mediacl help or contact a Poison Control Center right away.

Directions

- clean the infected area
- shake can well before using
- hold 6-8 inches from moist injured area
- spray until area is covered and superficial bleeding has stopped
- scab-like cover will gradually disappear or may be removed with soap and water
- for adult institutional use only
- not intended for use on children under 12 years of age

Other Information

- avoid inhaling
- use only as directed
- intentional misuse by deliberately concentrating and inhaling may be harmful or fatal
- store at room temperature 59-86•F (15-30•C)
- do not expose to temperatures above 120•F

Inactive Ingredients

isobutane, isopropyl myristate, karaya, n-butane, propane, silica, sorbitan monooloate, talc, tragacanth

Green Guard Super Stat Blood Clotter Spray

Super Stat

Blood Clotter Spray

- Aids in control of superficial bleeding
- Temporarily releives pain of minor cuts, burns and scrapes
- Helps prevent infection
- Contains no fluorocarbons

Green Guard®

Aerosol

WARNING: FLAMMABLE

Contents under Pressure, Read Back Panel Carefully

Net Wt. 3 oz. (85g)